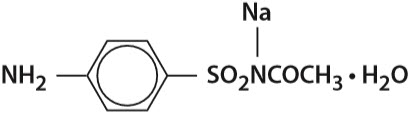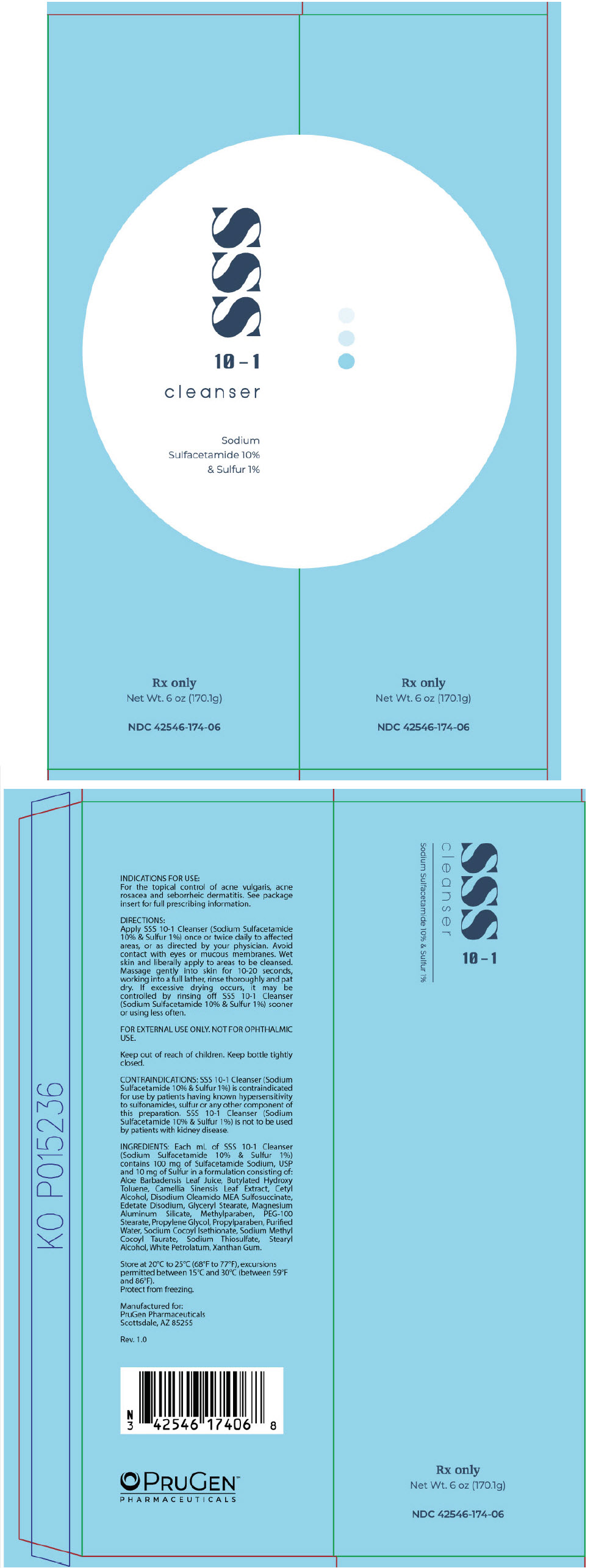 DRUG LABEL: SSS cleanser
NDC: 42546-174 | Form: CREAM
Manufacturer: PruGen Pharmaceuticals
Category: prescription | Type: HUMAN PRESCRIPTION DRUG LABEL
Date: 20220120

ACTIVE INGREDIENTS: SULFACETAMIDE SODIUM 100 mg/1 g; SULFUR 10 mg/1 g
INACTIVE INGREDIENTS: ALOE VERA LEAF; BUTYLATED HYDROXYTOLUENE; GREEN TEA LEAF; CETYL ALCOHOL; DISODIUM OLEAMIDO MONOETHANOLAMINE SULFOSUCCINATE; EDETATE DISODIUM; GLYCERYL MONOSTEARATE; MAGNESIUM ALUMINUM SILICATE; METHYLPARABEN; PEG-100 STEARATE; PROPYLENE GLYCOL; PROPYLPARABEN; WATER; SODIUM COCOYL ISETHIONATE; SODIUM METHYL COCOYL TAURATE; SODIUM THIOSULFATE; STEARYL ALCOHOL; PETROLATUM; XANTHAN GUM

SSS 10-1
cleanser
Sodium Sulfacetamide 10% & Sulfur 1%

Rx Only

Disclaimer: This drug has not been found by FDA to be safe and effective, and this labeling has not been approved by FDA.

DESCRIPTION

Sodium sulfacetamide is a sulfonamide with antibacterial activity while sulfur acts as a keratolytic agent. Chemically sodium sulfacetamide is N-[(4-aminophenyl) sulfonyl]-acetamide, monosodium salt, monohydrate. The structural formula is:

Each mL of SSS 10-1 Cleanser (Sodium Sulfacetamide 10% & Sulfur 1%) contains 100 mg of Sulfacetamide Sodium, USP and 10 mg of Sulfur in a formulation consisting of: Aloe Barbadensis Leaf Juice, Butylated Hydroxy Toluene, Camellia Sinensis Leaf Extract, Cetyl Alcohol, Disodium Oleamido MEA Sulfosuccinate, Edetate Disodium, Glyceryl Stearate, Magnesium Aluminum Silicate, Methylparaben, PEG-100 Stearate, Propylene Glycol, Propylparaben, Purified Water, Sodium Cocoyl Isethionate, Sodium Methyl Cocoyl Taurate, Sodium Thiosulfate, Stearyl Alcohol, White Petrolatum, Xanthan Gum.

CLINICAL PHARMACOLOGY

The most widely accepted mechanism of action of sulfonamides is the Woods-Fildes theory, which is based on the fact that sulfonamides act as competitive antagonists to para-aminobenzoic acid (PABA), an essential component for bacterial growth. While absorption through intact skin has not been determined, sodium sulfacetamide is readily absorbed from the gastrointestinal tract when taken orally and excreted in the urine, largely unchanged. The biological half-life has variously been reported as 7 to 12.8 hours. The exact mode of action of sulfur in the treatment of acne is unknown, but it has been reported that it inhibits the growth of Propionibacterium acnes and the formation of free fatty acids.

INDICATIONS

SSS 10-1 Cleanser (Sodium Sulfacetamide 10% & Sulfur 1%) is indicated for the topical control of acne vulgaris, acne rosacea and seborrheic dermatitis.

CONTRAINDICATIONS

SSS 10-1 Cleanser (Sodium Sulfacetamide 10% & Sulfur 1%) is contraindicated for use by patients having known hypersensitivity to sulfonamides, sulfur or any other component of this preparation. SSS 10-1 Cleanser (Sodium Sulfacetamide 10% & Sulfur 1%) is not to be used by patients with kidney disease.

WARNINGS

Although rare, sensitivity to sodium sulfacetamide may occur. Therefore, caution and careful supervision should be observed when prescribing this drug for patients who may be prone to hypersensitivity to topical sulfonamides. Systemic toxic reactions such as agranulocytosis, acute hemolytic anemia, purpura hemorrhagica, drug fever, jaundice, and contact dermatitis indicate hypersensitivity to sulfonamides. Particular caution should be employed if areas of denuded or abraded skin are involved.

FOR EXTERNAL USE ONLY. Keep away from eyes. Keep out of reach of children. Keep container tightly closed.

PRECAUTIONS

General

If irritation develops, use of the product should be discontinued and appropriate therapy instituted. Patients should be carefully observed for possible local irritation or sensitization during long-term therapy. The object of this therapy is to achieve desquamation without irritation, but sodium sulfacetamide and sulfur can cause reddening and scaling of the epidermis. These side effects are not unusual in the treatment of acne vulgaris, but patients should be cautioned about the possibility.

Information for Patients

Avoid contact with eyes, eyelids, lips and mucous membranes. If accidental contact occurs, rinse with water. If excessive irritation develops, discontinue use and consult your physician.

Carcinogenesis, Mutagenesis and Impairment of Fertility

Long-term studies in animals have not been performed to evaluate carcinogenic potential.

PREGNANCY

Category C

Animal reproduction studies have not been conducted with SSS 10-1 Cleanser (Sodium Sulfacetamide 10% & Sulfur 1%). It is also not known whether SSS 10-1 Cleanser (Sodium Sulfacetamide 10% & Sulfur 1%) can cause fetal harm when administered to a pregnant woman or can affect reproduction capacity. SSS 10-1 Cleanser (Sodium Sulfacetamide 10% & Sulfur 1%) should be given to a pregnant woman only if clearly needed.

NURSING MOTHERS

It is not known whether sodium sulfacetamide is excreted in the human milk following topical use of SSS 10-1 Cleanser (Sodium Sulfacetamide 10% & Sulfur 1%). However, small amounts of orally administered sulfonamides have been reported to be eliminated in human milk. In view of this and because many drugs are excreted in human milk, caution should be exercised when SSS 10-1 Cleanser (Sodium Sulfacetamide 10% & Sulfur 1%) is administered to a nursing woman.

PEDIATRIC USE

Safety and effectiveness in children under the age of 12 has not been established.

ADVERSE REACTIONS

Although rare, sodium sulfacetamide may cause local irritation.

DOSAGE AND ADMINISTRATION

Apply SSS 10-1 Cleanser (Sodium Sulfacetamide 10% & Sulfur 1%) once or twice daily to affected areas, or as directed by your physician. Wet skin and liberally apply to areas to be cleansed. Massage gently into skin for 10-20 seconds, working into a full lather, rinse thoroughly and pat dry. If drying occurs, it may be controlled by rinsing off SSS 10-1 Cleanser (Sodium Sulfacetamide 10% & Sulfur 1%) sooner or using less often.

HOW SUPPLIED

SSS 10-1 Cleanser (Sodium Sulfacetamide 10% & Sulfur 1%) is available in a 6 oz. (170.1g) tube, NDC 42546-174-06.

STORAGE AND HANDLING

Store at 20°C to 25°C (68°F to 77°F)

Protect from freezing.

KEEP THIS AND ALL MEDICATIONS OUT OF THE REACH OF CHILDREN.

Manufactured for:
PruGen Pharmaceuticals
Scottsdale, AZ 85255

Rev. 1.0

PRINCIPAL DISPLAY PANEL - 170.1 g Tube Carton

SSS
10-1
cleanser

Sodium
Sulfacetamide 10%
& Sulfur 1%

Rx only
Net Wt. 6 oz (170.1g)

NDC 42546-174-06